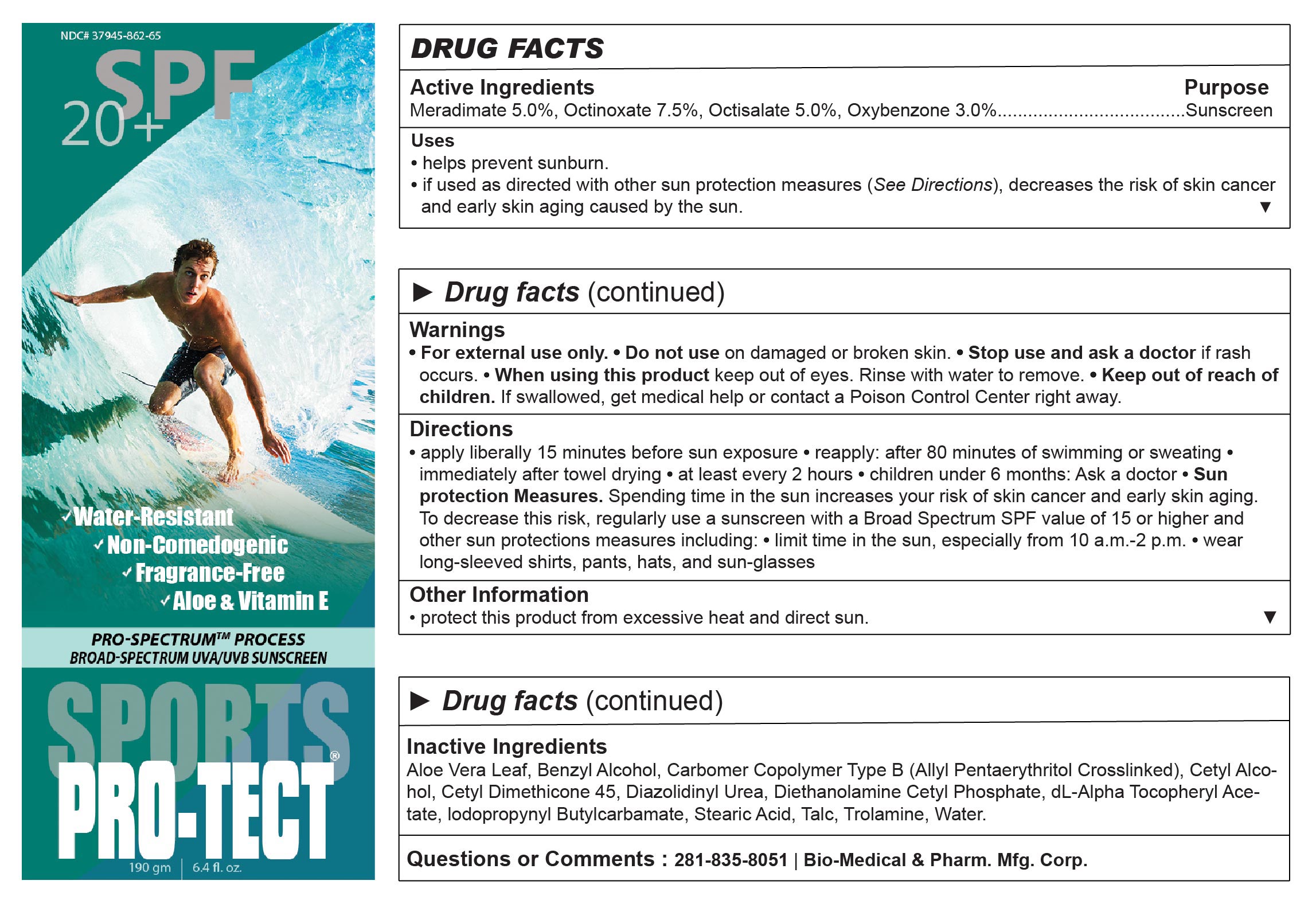 DRUG LABEL: PRO-TECT SPORTS SUNSCREEN
NDC: 37945-862 | Form: LOTION
Manufacturer: Bio-Medical & Pharmaceutical Manufacturing Corporation
Category: otc | Type: HUMAN OTC DRUG LABEL
Date: 20251203

ACTIVE INGREDIENTS: OCTINOXATE 75 mg/1 g; MERADIMATE 50 mg/1 g; OXYBENZONE 30 mg/1 g; OCTISALATE 50 mg/1 g
INACTIVE INGREDIENTS: WATER; ALOE VERA LEAF; IODOPROPYNYL BUTYLCARBAMATE; STEARIC ACID; TALC; TROLAMINE; BENZYL ALCOHOL; CARBOMER COPOLYMER TYPE B (ALLYL PENTAERYTHRITOL CROSSLINKED); CETYL ALCOHOL; CETYL DIMETHICONE 45; DIAZOLIDINYL UREA; DIETHANOLAMINE CETYL PHOSPHATE; .ALPHA.-TOCOPHEROL ACETATE, DL-

Active ingredients

Meradimate 5.0%

Octinoxate 7.5%

Octisalate 5.0%

Oxybenzone 3.0%

Purpose

Sunscreen

Uses

•helps prevent sunburn.
•if used as directed with other sun protection measures (see Directions), decreases the risk of skin cancer and early skin aging caused by the sun.

Warnings

- For external use only.
- Do not use on damaged or broken skin.
- Stop use and ask a doctor if rash occurs.
- When using this product keep out of eyes. Rinse with water to remove.
- Keep out of reach of children. If swallowed, get medical help or contact a Poison Control Center right away.

Directions

•apply liberally 15 minutes before sun exposure
•reapply: •after 80 minutes of swimming or sweating •immediately after towel drying •at least every 2 hours
•children under 6 months: Ask a doctor
•Sun Protection Measures. Spending time in the sun increases your risk of skin cancer and early skin aging. To decrease this risk, regularly use a sunscreen with a Broad Spectrum SPF value of 15 or higher and other sun protection measures including: •limit time in the sun, especially from 10 a.m.–2 p.m. •wear long-sleeved shirts, pants, hats, and sun-glasses

Other Information

•protect this product from excessive heat and direct sun.

Inactive Ingredients

Aloe Vera Leaf, Benzyl Alcohol, Carbomer Copolymer Type B (Allyl Pentaerythritol Crosslinked), Cetyl Alcohol, Cetyl Dimethicone 45, Diazolidinyl Urea, Diethanolamine Cetyl Phosphate, dl-Alpha Tocopheryl Acetate, Iodopropynyl Butylcarbamate, Stearic Acid, Talc, Trolamine, Water.

Questions or Comments

281-835-8051

Bio-Medical & Pharm. Mfg. Corp.

RECENT MAJOR CHANGES

uses 07/2021

directions 07/2021

Package label

pro-tect spf 20 6.4 oz